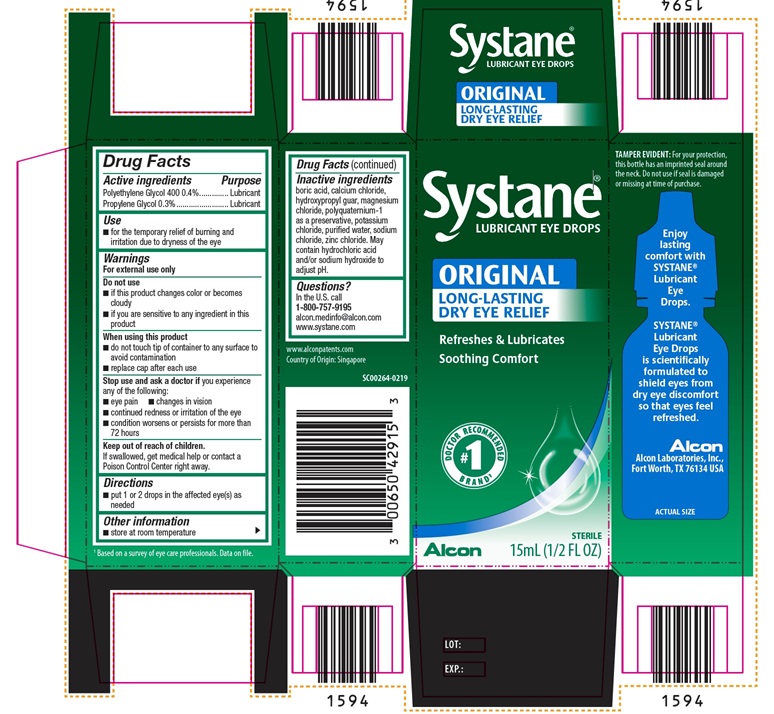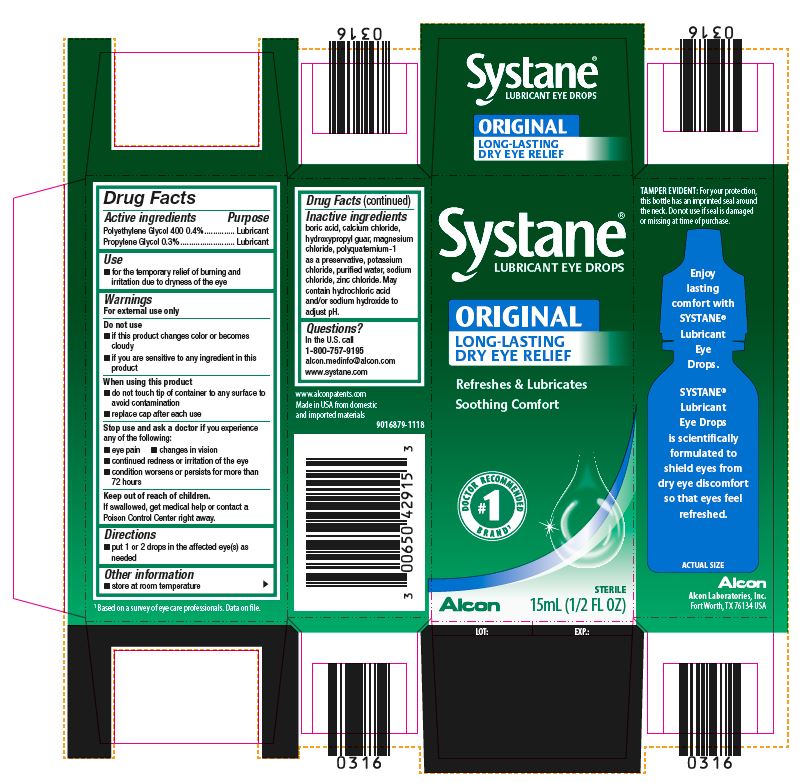 DRUG LABEL: Systane Lubricant
NDC: 0065-0429 | Form: SOLUTION/ DROPS
Manufacturer: Alcon Laboratories, Inc.
Category: otc | Type: HUMAN OTC DRUG LABEL
Date: 20231215

ACTIVE INGREDIENTS: Polyethylene Glycol 400 4 mg/1 mL; Propylene Glycol 3 mg/1 mL
INACTIVE INGREDIENTS: Boric Acid; Calcium Chloride; Guar Gum; Magnesium Chloride; Polidronium Chloride; Potassium Chloride; Water; Sodium Chloride; Zinc Chloride; Hydrochloric Acid; Sodium Hydroxide

Drug Facts

ACTIVE INGREDIENT

Active Ingredients | Purpose
Polyethylene Glycol 400 0.4% | Lubricant
Propylene Glycol 0.3% | Lubricant

Uses

- For the temporary relief of burning and irritation due to dryness of the eye

Warnings

For external use only

Do not use

- if this product changes color or becomes cloudy
- if you are sensitive to any ingredient in this product

When using this product

- do not touch tip of container to any surface to avoid contamination
- replace cap after each use

Stop use and ask a doctor if you experience any of the following:

- eye pain
- changes in vision
- continued redness or irritation of the eye
- condition worsens or persists for more than 72 hours

Keep out of reach of children.
If swallowed, get medical help or contact a Poison Control Center right away.

Directions

- put 1 or 2 drops in the affected eye(s) as needed

Other Information

- store at room temperature

Inactive Ingredients:

Boric acid, calcium chloride, hydroxypropyl guar, magnesium chloride, polyquaternium-1 as a preservative, potassium chloride, purified water, sodium chloride, zinc chloride. May contain hydrochloric acid and/or sodium hydroxide to adjust pH.

Questions?

In the U.S. call 1-800-757-9195
alcon.medinfo@alcon.com
www.systane.com

PRINCIPAL DISPLAY PANEL

Systane®
LUBRICANT EYE DROPS
ORIGINAL
LONG-LASTING
DRY EYE RELIEF
Refreshes & Lubricates
Soothing Comfort
#1 DOCTOR RECOMMENDED BRAND^1
Alcon
STERILE
15 mL (1/2 FL OZ)
SIDE PANEL
TAMPER EVIDENT: For your protection, this bottle has an imprinted seal around the neck. Do not use if seal is damaged or missing at time of purchase.
Enjoy lasting comfort with SYSTANE® Lubricant Eye Drops.
SYSTANE® Lubricant Eye Drops is scientifically formulated to shield eyes from dry eye discomfort so that eyes feel refreshed.
ACTUAL SIZE
Alcon
Alcon Laboratories, Inc.
Fort Worth, TX 76134 USA
^1Based on a survey of eye care professionals. Data on file.
www.alconpatents.com
Made in USA from domestic and imported materials
9016879-1118
LOT: EXP:

Systane®
LUBRICANT EYE DROPS
ORIGINAL LONG-LASTING
DRY EYE RELIEF
Refreshes & Lubricates
Soothing Comfort
#1 DOCTOR RECOMMENDED BRAND^1
Alcon
STERILE
15 mL (1/2 FL OZ)
SIDE PANEL
TAMPER EVIDENT: For your protection, this bottle has an imprinted seal around the neck. Do not use if seal is damaged or missing at time of purchase.
Enjoy lasting comfort with SYSTANE® Lubricant Eye Drops.
SYSTANE® Lubricant Eye Drops is scientifically formulated to shield eyes from dry eye discomfort so that eyes feel refreshed.
ACTUAL SIZE
Alcon
Alcon Laboratories, Inc.
Fort Worth, TX 76134 USA
^1Based on a survey of eye care professionals. Data on file.
www.alconpatents.com
Country of Origin: Singapore
SC00264-0219
LOT: EXP: